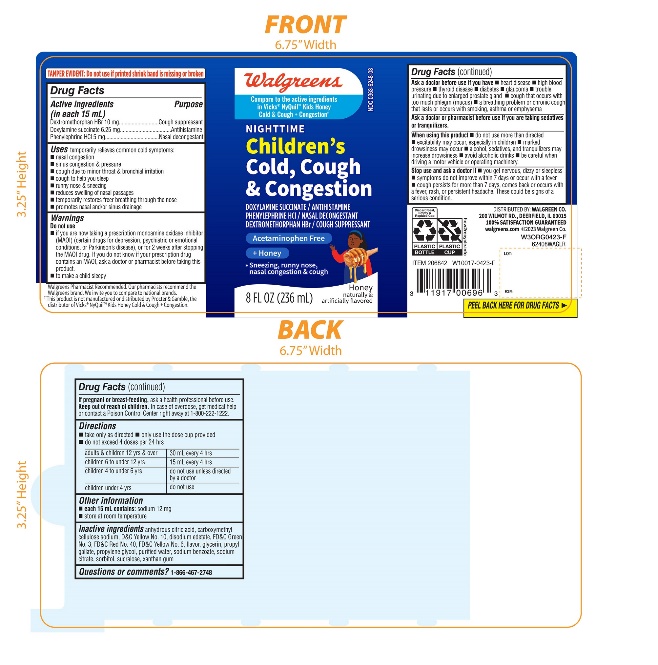 DRUG LABEL: Walgreens Nighttime Kids

NDC: 0363-6248 | Form: LIQUID
Manufacturer: WALGREENS CO
Category: otc | Type: HUMAN OTC DRUG LABEL
Date: 20251201

ACTIVE INGREDIENTS: DEXTROMETHORPHAN HYDROBROMIDE 10 mg/15 mL; DOXYLAMINE SUCCINATE 6.25 mg/15 mL; PHENYLEPHRINE HYDROCHLORIDE 5 mg/15 mL
INACTIVE INGREDIENTS: ANHYDROUS CITRIC ACID; CARBOXYMETHYLCELLULOSE SODIUM, UNSPECIFIED; EDETATE DISODIUM; D&C YELLOW NO. 10; FD&C GREEN NO. 3; FD&C RED NO. 40; FD&C YELLOW NO. 6; GLYCERIN; PROPYL GALLATE; PROPYLENE GLYCOL; WATER; SODIUM CITRATE, UNSPECIFIED FORM; SODIUM BENZOATE; SORBITOL; SUCRALOSE; XANTHAN GUM

Walgreens Nighttime Kids Cold & Cough + Congestion

Drug Facts

Active ingredients (in each 15 mL)

Dextromethorphan HBr 10 mg

Doxylamine succinate 6.25 mg

Phenylephrine HCl 5 mg

Purpose

Cough suppressant

Antihistamine

Nasal decongestant

Uses

temporarily relieves common cold symptoms:

- nasal congestion
- sinus congestion & pressure
- cough due to minor throat & bronchial irritation
- cough to help you sleep
- runny nose & sneezing
- reduces swelling of nasal passages
- temporarily restores freer breathing through the nose
- promotes nasal and/or sinus drainage

Warnings

Do not use

- if you are now taking a prescription monoamine oxidase inhibitor (MAOI) (certain drugs for depression, psychiatric or emotional conditions, or Parkinson's disease), or for 2 weeks after stopping the MAOI drug. If you do not know if your prescription drug contains an MAOI, ask a doctor or pharmacist before taking this product.
- to make a child sleepy

Ask a doctor before use if you have

- heart disease
- high blood pressure
- thyroid disease
- diabetes
- glaucoma
- trouble urinating due to enlarged prostate gland
- cough that occurs with too much phlegm (mucus)
- a breathing problem or chronic cough that lasts or as occurs with smoking, asthma, or emphysema

Ask a doctor or pharmacist before use if you are

taking sedatives or tranquilizers

When using this product

- do not use more than directed.
- excitability may occur, especially in children
- marked drowsiness may occur
- alcohol, sedatives, and tranquilizers may increase drowsiness
- avoid alcoholic drinks
- be careful when driving a motor vehicle or operating machinery

Stop use and ask a doctor if

- you get nervous, dizzy or sleepless
- symptoms do not improve within 7 days or occur with a fever
- cough persists for more than 7 days, comes back or occurs with a fever, rash or persistent headache.

These could be signs of a serious condition.

PREGNANCY OR BREAST FEEDING

If pregnant or breast-feeding, ask a health professional before use.

Keep out of reach of children.

Overdose warning

In case of overdose, get medical help or contact a Poison Control Center right away at 1-800-222-1222.

Directions

- take only as directed
- only use dose cup provided
- do not exceed 4 doses per 24 hrs

adults & children 12 yrs & over | 30 mL every 4 hrs
children 6 to under 12 yrs | 15 mL every 4 hrs
children 4 to under 6 yrs | do not use unless directed by a doctor
children under 4 yrs | do not use

Other information

- each 15 mL contains:sodium 12 mg
- store at room temperature

Inactive ingredients

Anhydrous citric acid, carboxymethylcellulose sodium, disodium edetate, D&C Yellow No. 10, FD&C Green No. 3, FD&C Red No. 40, FD&C Yellow No. 6, flavor, glycerin, propyl gallate, propylene glycol, purified water, sodium benzoate, sodium citrate, sorbitol, sucralose, , xanthan gum

Questions?

1-866-467-2748

Distributed by:

PRINCIPAL DISPLAY PANEL - 236 ml Bottle Label

Compare to the active ingredients in Kids Vicks®NyQuil™ Honey Cold & Cough + Congestion*

NDC 0363-6248-08

Nighttime

Kid’s

Cold & Cough + Congestion

Doxylamine Succinate, Phenylephrine HCl, Dextromethorphan HBr

- Sneezing, Runny Nose
- Nasal Congestion
- Cough

No Added Alcohol & Acetaminophen Free

Honey Flavor

Naturally and Artificially Flavored

8 FL OZ (236 mL)

*This Product is not manufactured or distributed by Procter & Gamble, the distributor of Kids Vicks®NyQuil™ Honey Cold & Cough + Congestion.